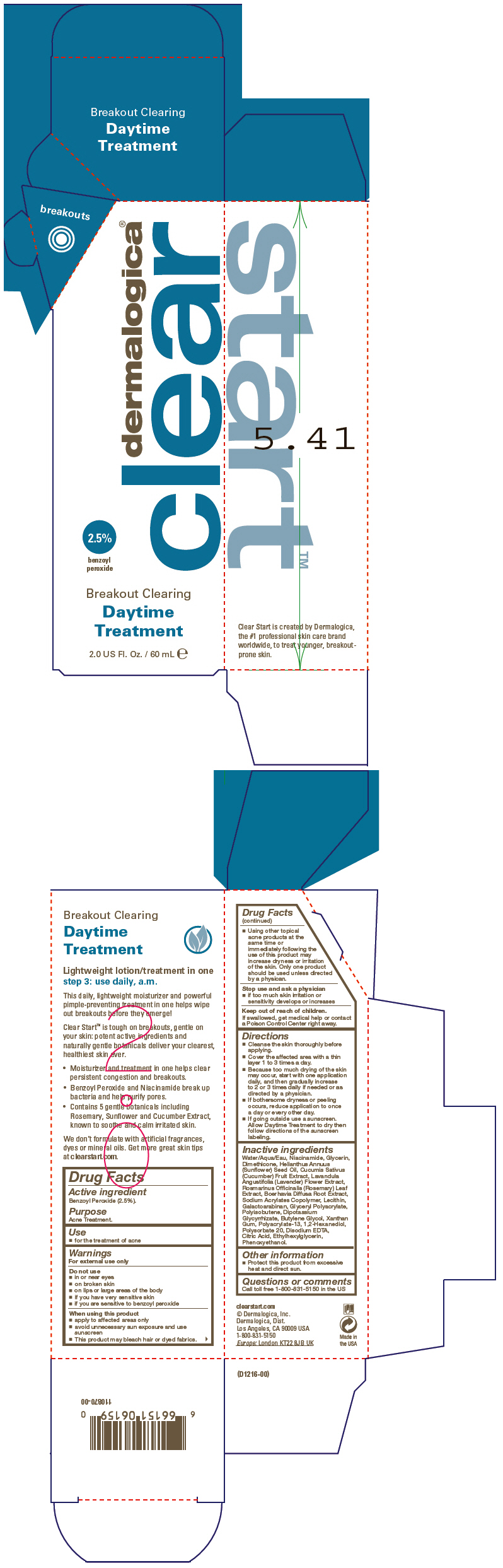 DRUG LABEL: Breakout Clearing Daytime Treatment
NDC: 68479-160 | Form: LOTION
Manufacturer: Dermalogica, Inc.
Category: otc | Type: HUMAN OTC DRUG LABEL
Date: 20151124

ACTIVE INGREDIENTS: Benzoyl Peroxide 25 mg/1 mL
INACTIVE INGREDIENTS: Water; Niacinamide; Glycerin; Dimethicone; Sunflower Oil; Cucumber; Lavandula Angustifolia Flowering Top; Rosemary; Boerhavia Diffusa Root; Glycyrrhizinate Dipotassium; Egg Phospholipids; Galactoarabinan; Polyisobutylene (1300 MW); Butylene Glycol; Xanthan Gum; 1,2-Hexanediol; Polysorbate 20; Edetate Disodium; Citric Acid Monohydrate; Phenoxyethanol; Ethylhexylglycerin

Breakout Clearing Daytime Treatment

Drug Facts

Active ingredient

Benzoyl Peroxide (2.5%).

Purpose

Acne Treatment.

Use

- for the treatment of acne

Warnings

For external use only

Do not use

- in or near eyes
- on broken skin
- on lips or large areas of the body
- if you have very sensitive skin
- if you are sensitive to benzoyl peroxide

When using this product

- apply to affected areas only
- avoid unnecessary sun exposure and use sunscreen
- This product may bleach hair or dyed fabrics.
- Using other topical acne products at the same time or immediately following the use of this product may increase dryness or irritation of the skin. Only one product should be used unless directed by a physican.

Stop use and ask a physician

- if too much skin irritation or sensitivity develops or increases

Keep out of reach of children.

If swallowed, get medical help or contact a Poison Control Center right away.

Directions

- Cleanse the skin thoroughly before applying.
- Cover the affected area with a thin layer 1 to 3 times a day.
- Because too much drying of the skin may occur, start with one application daily, and then gradually increase to 2 or 3 times daily if needed or as directed by a physician.
- If bothersome dryness or peeling occurs, reduce application to once a day or every other day.
- If going outside use a sunscreen. Allow Daytime Treatment to dry then follow directions of the sunscreen labeling.

Inactive ingredients

Water/Aqua/Eau, Niacinamide, Glycerin, Dimethicone, Helianthus Annuus (Sunflower) Seed Oil, Cucumis Sativus (Cucumber) Fruit Extract, Lavandula Angustifolia (Lavender) Flower Extract, Rosmarinus Officinalis (Rosemary) Leaf Extract, Boerhavia Diffusa Root Extract, Sodium Acrylates Copolymer, Lecithin, Galactoarabinan, Glyceryl Polyacrylate, Polyisobutene, Dipotassium Glycyrrhizate, Butylene Glycol, Xanthan Gum, Polyacrylate-13, 1,2-Hexanediol, Polysorbate 20, Disodium EDTA, Citric Acid, Ethylhexylglycerin, Phenoxyethanol.

Other information

- Protect this product from excessive heat and direct sun.

Questions or comments

Call toll free 1-800-831-5150 in the US

PRINCIPAL DISPLAY PANEL - 60 mL Tube Carton

dermalogica®
clear

2.5%
benzoyl
peroxide

Breakout Clearing
Daytime
Treatment

2.0 US Fl. Oz. / 60 mL e